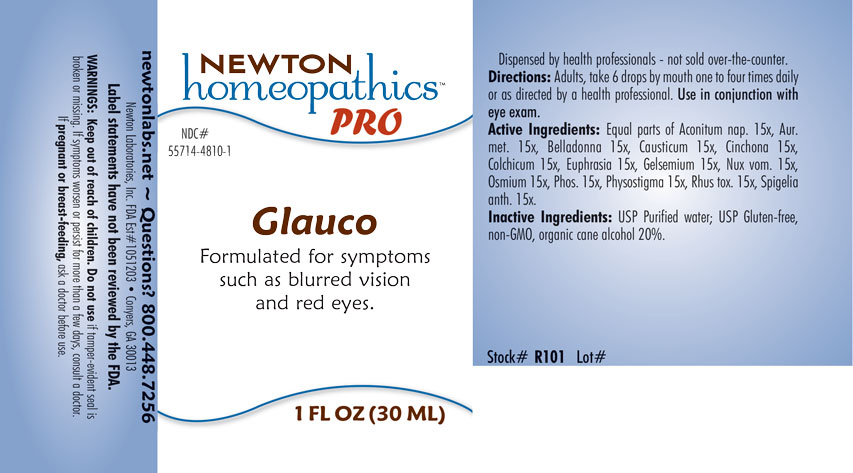 DRUG LABEL: Glauco
NDC: 55714-4810 | Form: LIQUID
Manufacturer: Newton Laboratories, Inc.
Category: homeopathic | Type: HUMAN OTC DRUG LABEL
Date: 20201203

ACTIVE INGREDIENTS: ACONITUM NAPELLUS 15 [hp_X]/1 mL; ATROPA BELLADONNA 15 [hp_X]/1 mL; CAUSTICUM 15 [hp_X]/1 mL; CINCHONA OFFICINALIS BARK 15 [hp_X]/1 mL; COLCHICUM AUTUMNALE BULB 15 [hp_X]/1 mL; EUPHRASIA STRICTA 15 [hp_X]/1 mL; GELSEMIUM SEMPERVIRENS ROOT 15 [hp_X]/1 mL; STRYCHNOS NUX-VOMICA SEED 15 [hp_X]/1 mL; OSMIUM 15 [hp_X]/1 mL; PHOSPHORUS 15 [hp_X]/1 mL; PHYSOSTIGMA VENENOSUM SEED 15 [hp_X]/1 mL; TOXICODENDRON PUBESCENS LEAF 15 [hp_X]/1 mL; SPIGELIA ANTHELMIA 15 [hp_X]/1 mL; GOLD 15 [hp_X]/1 mL
INACTIVE INGREDIENTS: WATER; ALCOHOL

Glauco 4810L

INDICATIONS & USAGE SECTION

Formulated for symptoms such as blurred vision and red eyes..

DOSAGE & ADMINISTRATION SECTION

Directions: Adults take 6 drops by mouth one to four times daily or as directed by a health professional. Use in conjunction with eye exam.

OTC - ACTIVE INGREDIENT SECTION

Equal parts of Aconitum napellus 15x, Aurum metallicum 15x, Belladonna 15x, Causticum 15x, Cinchona officinalis 15x, Colchicum autumnale 15x, Euphrasia officinalis 15x, Gelsemium sempervirens 15x, Nux vomica 15x, Osmium metallicum 15x, Phosphorus 15x, Physostigma venenosum 15x, Rhus toxicodendron 15x, Spigelia anthelmia 15x.

OTC - PURPOSE SECTION

Formulated for symptoms such as blurred vision and red eyes.

INACTIVE INGREDIENT SECTION

Inactive Ingredients: USP Purified Water; USP Gluten-free, non-GMO, organic cane alcohol 20%.

QUESTIONS SECTION

newtonlabs.net - Questions? 800.448.7256

Newton Laboratories, Inc. FDA Est # 1051203 Conyers, GA 30013

WARNINGS SECTION

WARNINGS: Keep out of reach of children. Do not use if tamper-evident seal is broken or missing. If symptoms worsen or persist for more than a few days, consult a doctor. If pregnant or breast-feeding, ask a doctor before use.

OTC - PREGNANCY OR BREAST FEEDING SECTION

If pregnant or breast-feeding, ask a doctor before use.

OTC - KEEP OUT OF REACH OF CHILDREN SECTION

Keep out of reach of children.